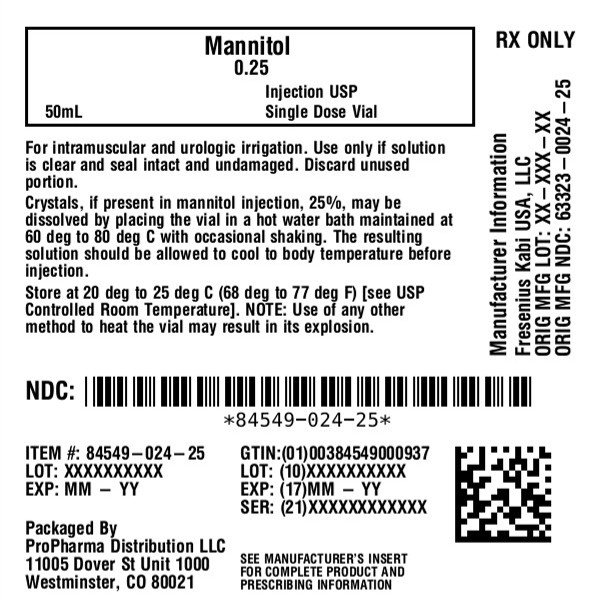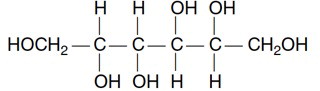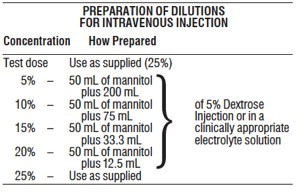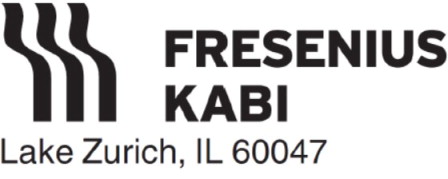 DRUG LABEL: Mannitol
NDC: 84549-024 | Form: INJECTION, SOLUTION
Manufacturer: ProPharma Distribution
Category: prescription | Type: HUMAN PRESCRIPTION DRUG LABEL
Date: 20251107

ACTIVE INGREDIENTS: MANNITOL 250 mg/1 mL

Mannitol Injection, USP

Rx only

25%

For Intravenous Use and Urologic Irrigation

DESCRIPTION

Mannitol is a 6-carbon sugar alcohol and has the following structure:

C6 H14 O 6 182.17

Mannitol occurs naturally in fruits and vegetables, and is metabolically inert in humans.

Mannitol Injection, USP, 25%, an osmotic diuretic, is a sterile, nonpyrogenic solution of mannitol in Water for Injection. It is a supersaturated solution at room temperature.

Each mL contains: Mannitol 250 mg; Water for Injection q.s. The osmolar concentration is 1372 mOsmol/L (calc.). It contains no antimicrobial agents. The pH of a 5% solution is between 4.5 and 7.0.

CLINICAL PHARMACOLOGY

Mannitol is an osmotic diuretic. After intravenous injection it is confined to the extracellular space, metabolized only slightly and excreted rapidly by the kidneys. Approximately 80% of a 100 g dose appears in the urine in three hours. Mannitol is freely filtered by the glomeruli with less than 10% tubular reabsorption. It is not secreted by tubular cells. It induces diuresis by elevating the osmolarity of the glomerular filtrate and thereby hinders tubular reabsorption of water. Urinary output of water and excretion of sodium and chloride are enhanced. Mannitol is poorly absorbed from the gastrointestinal tract.

Mannitol injection is free of electrolytes and is used in urology as a nonhemolytic irrigant. The amount of mannitol absorbed intravascularly during transurethral prostatic surgery is variable and depends primarily on the extent of the surgery. Such mannitol is excreted by the kidneys and produces osmotic diuresis.

INDICATIONS AND USAGE

For Intravenous Injection

Mannitol Injection, USP is indicated for the following therapeutic uses:

• The promotion of diuresis, in the prevention and/or treatment of the oliguric phase of acute renal failure before irreversible renal failure becomes established.

• The reduction of intracranial pressure and treatment of cerebral edema by reducing brain mass.

• The reduction of elevated intraocular pressure when it cannot be lowered by other means.

• The promotion of urinary excretion of toxic substances.

For Urologic Irrigation

Mannitol solution, 2.5% is indicated as an irrigation solution in transurethral prostatic resection or other transurethral surgical procedures.

CONTRAINDICATIONS

• Well established anuria due to severe renal disease.

• Severe pulmonary congestion or frank pulmonary edema.

• Active intracranial bleeding except during craniotomy.

• Severe dehydration.

• Progressive renal damage or dysfunction after institution of mannitol therapy, including increasing oliguria and azotemia.

• Progressive heart failure or pulmonary congestion after mannitol therapy is started.

WARNINGS

In severe impairment of renal function a test dose should be given (see DOSAGE AND ADMINISTRATION). A second test dose may be given if there is an inadequate response. No more than two test doses should be attempted.

Excessive loss of water and electrolytes may lead to serious imbalances. Serum sodium and potassium should be carefully monitored during mannitol therapy.

The diuresis after rapid infusion of mannitol may increase preexisting hemoconcentration. With continued use of mannitol a loss of water in excess of electrolytes can cause hypernatremia.

Shift of sodium-free intracellular fluid into the extracellular compartment after mannitol infusion may lower serum sodium concentration and aggravate preexisting hyponatremia.

Closely monitor the urine output and discontinue mannitol infusion promptly if output is low. Inadequate urine output results in accumulation of mannitol, expansion of extracellular fluid volume and could result in water intoxication or congestive heart failure. Renal function must be closely monitored during mannitol infusion.

Mannitol solution must be used with caution in patients with significant cardiopulmonary or renal dysfunction.

Irrigating solutions used in transurethral prostatectomy have been shown to enter the systemic circulation in relatively large volumes, exert a systemic effect and may significantly alter cardiopulmonary and renal dynamics.

PRECAUTIONS

General

Crystals, if present in mannitol injection, 25%, may be dissolved by placing the vial in a hot water bath maintained at 60° to 80°C with occasional shaking. The resulting solution should be allowed to cool to body temperature before injection.

An administration set with a filter should be used for intravenous infusions of solutions containing 20% or more of mannitol.

NOTE: Use of any other method to heat the vial may result in its explosion.

The cardiovascular status should be carefully evaluated before mannitol is administered by rapid intravenous injection or before and during transurethral resection since expansion of extracellular fluid may lead to fulminating congestive heart failure.

By sustaining diuresis, mannitol may obscure and intensify inadequate hydration or hypovolemia.

Unless it is essential, electrolyte-free mannitol solutions should not be combined with blood. When it is essential to give the combination, at least 20 mEq of sodium chloride should be added to each liter of mannitol solution to avoid pseudoagglutination. The contents of opened containers should be used promptly and unused contents should be discarded.

A white flocculant mannitol precipitate may result from contact with PVC surfaces which act as nuclei for rapid rate crystallization of small crystals. This condition has also been reported to occur when mannitol has come in contact with other plastic and rough glass surfaces. Attempting to resolubilize the white flocculant precipitate with the aid of heat is not useful because crystallization may recur in a short period of time.

Carcinogenesis, Mutagenesis, Impairment of Fertility

In an early study of 1, 5 or 10% mannitol, given for 94 weeks in the diet of Wistar rats, a low incidence of benign thymomas occurred in females which was apparently treatment related. A subsequent life-time study at similar dose levels in Spraque-Dawley, Fischer and Wistar rats revealed no carcinogenic effect in the thymus.

Mannitol had no mutagenic activity in a series of in vitroand in vivotest systems.

Adequate studies measuring the effects of mannitol on fertility have not been done.

Pregnancy

Pregnancy Category B–Teratogenic studies in the mouse, rat and rabbit at oral doses up to 1600 mg/kg did not reveal harm to the fetus or adverse effects on reproduction due to mannitol. There are, however, no adequate and well-controlled studies in pregnant women. Because animal reproduction studies are not always predictive of human response, this drug should be used during pregnancy only if clearly needed.

Nursing Mothers

It is not known whether this drug is excreted in human milk. Because many drugs are excreted in human milk, caution should be exercised when mannitol is given to a nursing mother.

Pediatric Use

Dosage requirements in children below the age of 12 years have not been established.

ADVERSE REACTIONS

Reactions are infrequent and may include:

To report SUSPECTED ADVERSE REACTIONS, contact Fresenius Kabi USA, LLC at 1-800-551-7176 or FDA at 1-800-FDA-1088 or www.fda.gov/medwatch.

Metabolic:fluid and electrolyte imbalance, acidosis, dehydration.

Gastrointestinal:dryness of mouth, nausea, vomiting, diarrhea.

Genitourinary:osmotic nephrosis, urinary retention.

Central Nervous System:headache, convulsions, dizziness.

Special Senses:Blurred vision, rhinitis.

Cardiovascular:pulmonary edema, edema, hypotension, hypertension, tachycardia, angina-like chest pains.

Dermatologic:skin necrosis, thrombophlebitis.

Hypersensitivity:urticaria.

Miscellaneous:thirst, arm pain, chills, fever.

DOSAGE AND ADMINISTRATION

For Intravenous Injection

General Recommendations–Give mannitol injection only intravenously. The total dosage, concentration and rate of administration should be governed by the nature and severity of the condition being treated, fluid requirement and urinary output. Usual adult dosage ranges from 50 to 200 g in 24 hours but in most instances an adequate response will be achieved at a dosage of approximately 100 g in 24 hours. The rate is usually adjusted to maintain an adequate urine flow (at least 30 to 50 mL/hr).

Test Dose–In marked oliguria or inadequate renal function a test dose of mannitol should be given. The test dose may be approximately 0.2 g/kg (about 50 mL of a 25% solution) infused in three to five minutes to produce an adequate urine flow (at least 30 to 50 mL/hr). If urine flow does not increase within two or three hours a second test dose may be given. If there is an inadequate response the patient should be reevaluated.

Prevention of Acute Renal Failure (Oliguria)–When used during surgery, immediately postoperatively or following trauma, 50 to100 g of mannitol as a 5 to 25% solution maybe given. The concentration and amount will depend upon the fluid requirements of the patient. Following suspected or actual hemolytic transfusion reactions 20 g of mannitol may be given intravenously over a five minute period to provoke diuresis. If diuresis does not occur the 20 g dose may be repeated. If there is an adequate urine flow (30 to 50 mL/hr) then intravenous fluids containing not more than 50 to 75 mEq of sodium per liter should be given in sufficient volume to match the desired urine flow (100 mL/hr) until fluids can be taken orally.

Treatment of Oliguria–The usual dose for treatment of oliguria is 50 to 100 g as a 15 to 25% solution.

Reduction of Intracranial Pressure, Cerebral Edema or Intraocular Pressure–A 25% solution of mannitol is recommended since its effectiveness depends on establishing intravascular hyperosmolarity. When used before or after surgery, a total dose of 1.5 to 2 g/kg can be given over a period of 30 to 60 minutes. Careful evaluation must be made of the circulatory and renal reserve prior to and during use of mannitol at this relatively high dose and rapid infusion rate. Careful attention must be paid to fluid and electrolyte balance, body weight, and total input and output before and after infusion of mannitol. Evidence of reduced cerebral spinal fluid pressure may be observed within 15 minutes after starting infusion.

Maximal reduction of intraocular pressure occurs 30 to 60 minutes after injection.

Urinary Excretion of Toxic Substances–Mannitol in 5 to 25% solutions is used as an infusion as long as indicated if the level of urinary output remains high. The concentration will depend upon the fluid requirement and urinary output. Intravenous water and electrolytes must be given to replace the loss of these substances in the urine, sweat and expired air. If benefits are not observed after 200 g of mannitol are given, discontinue it.

For Urologic Irrigation

A 2.5% solution is used. The use of 2.5% mannitol solution minimizes the hemolytic effect of water alone, the entrance of hemolyzed blood into the circulation, and the resulting hemoglobinemia which is considered a major factor in producing serious renal complications.

PREPARATION OF DILUTIONS
FOR UROLOGIC IRRIGATION
Concentration | How Prepared
2.5% | Add contents of two 50 mL vials (25% mannitol) to 900 mL Sterile Water for Injection.

HOW SUPPLIED:

Mannitol Injection, USP, 25%

 | Unit of Sale | Strength | Each
 | NDC; 84549-024-25 | 250 mg per mL | 50 mL Single Dose Flip-off Top Vial

Use only if solution is clear and seal intact and undamaged.

Store at 20° to 25°C (68° to 77°F) [see USP Controlled Room Temperature].

Preservative Free. Discard unused portion.

www.fresenius-kabi.com/us